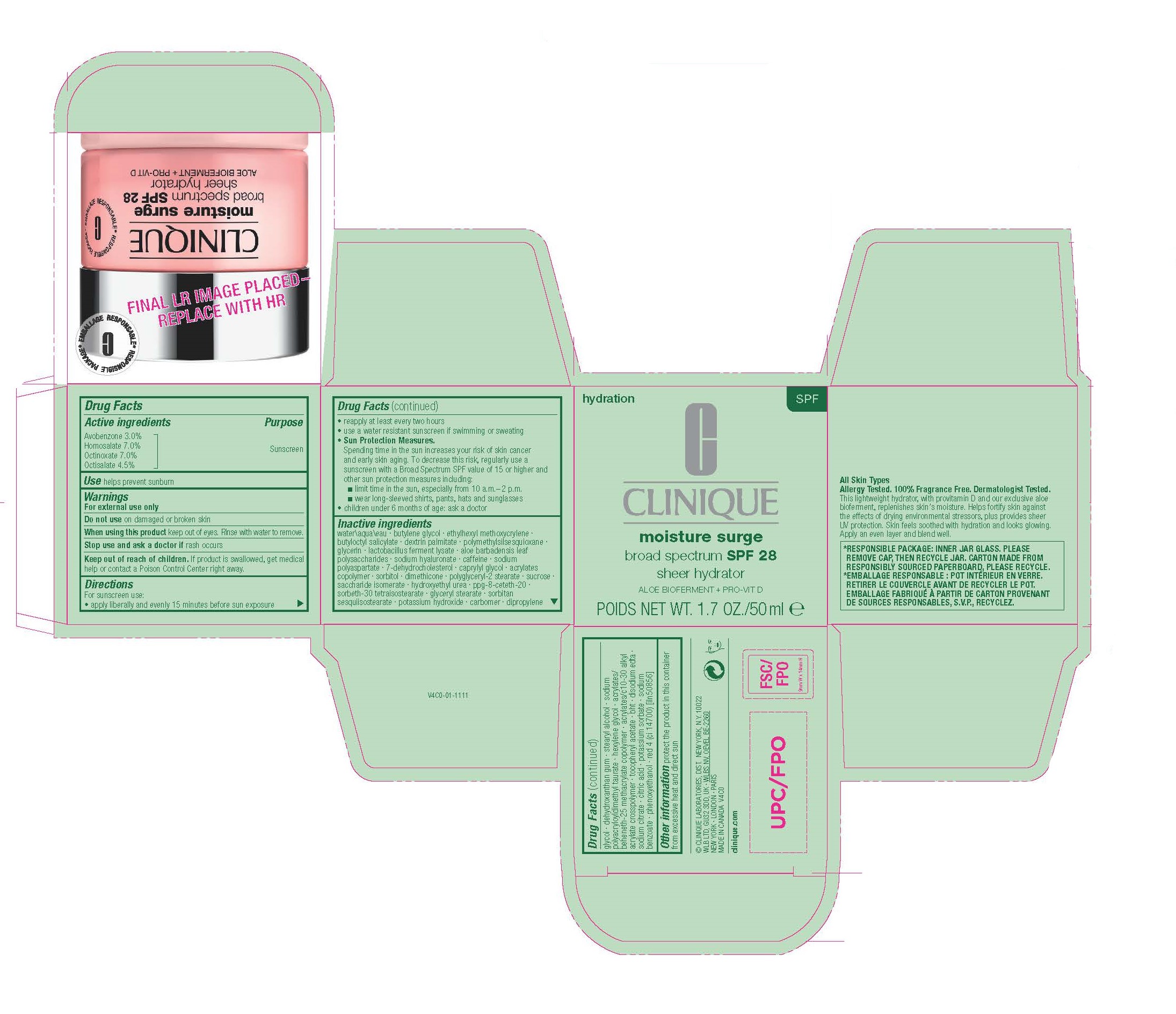 DRUG LABEL: MOISTURE SURGE SPF
NDC: 49527-084 | Form: CREAM
Manufacturer: CLINIQUE LABORATORIES LLC
Category: otc | Type: HUMAN OTC DRUG LABEL
Date: 20250815

ACTIVE INGREDIENTS: HOMOSALATE 70 mg/1 mL; OCTINOXATE 70 mg/1 mL; OCTISALATE 45 mg/1 mL; AVOBENZONE 30 mg/1 mL
INACTIVE INGREDIENTS: METHACRYLIC ACID AND ETHYL ACRYLATE COPOLYMER; WATER; ALOE VERA LEAF POLYSACCHARIDES; 7-DEHYDROCHOLESTEROL; CAPRYLYL GLYCOL; SORBITOL; POLYGLYCERYL-2 STEARATE; DISODIUM ASPARTATE; SACCHARIDE ISOMERATE; .ALPHA.-TOCOPHEROL ACETATE; POTASSIUM SORBATE; DEHYDROXANTHAN GUM; POLYMETHYLSILSESQUIOXANE (4.5 MICRONS); DIMETHICONE; SODIUM BENZOATE; PHENOXYETHANOL; ETHYLHEXYL METHOXYCRYLENE; SUCROSE; PPG-8-CETETH-20; GLYCERYL MONOSTEARATE; SORBITAN SESQUIISOSTEARATE; HEXYLENE GLYCOL; EDETATE DISODIUM ANHYDROUS; SODIUM CITRATE; CITRIC ACID MONOHYDRATE; HYDROXYETHYL UREA; POTASSIUM HYDROXIDE; CARBOMER HOMOPOLYMER, UNSPECIFIED TYPE; DIPROPYLENE GLYCOL; BUTYLATED HYDROXYTOLUENE; CAFFEINE; STEARYL ALCOHOL; GLYCERIN; BUTYLOCTYL SALICYLATE; BUTYLENE GLYCOL; LIMOSILACTOBACILLUS FERMENTUM; HYALURONATE SODIUM; DEXTRIN PALMITATE (CORN; 20000 MW); FD&C RED NO. 4

MOISTURE SURGE SPF

ACTIVE INGREDIENTS

Avobenzone 3.0%
Homosalate 7.0%
Octinoxate 7.0%
Octisalate 4.5%

PURPOSE

SUNSCREEN

USE

helps prevent sunburn

WARNINGS

DO NOT USE

on damaged or broken skin

WHEN USING THIS PRODUCT

Keep out of eyes. Rinse with water to remove

STOP USE AND ASK A DOCTOR

if rash occurs

KEEP OUT OF REACH OF CHILDREN

If product is swallowed, get medical help or contact a Poison Control Center right away.

DIRECTIONS

For sunscreen use:
• apply liberally and evenly 15 minutes before sun exposure

reapply at least every two hours
• use a water resistant sunscreen if swimming or sweating
• Sun Protection Measures.
Spending time in the sun increases your risk of skin cancer
and early skin aging. To decrease this risk, regularly use a
sunscreen with a Broad Spectrum SPF value of 15 or higher and
other sun protection measures including:
■ limit time in the sun, especially from 10 a.m.–2 p.m.
■ wear long-sleeved shirts, pants, hats and sunglasses
• children under 6 months of age: ask a doctor

INACTIVE INGREDIENTS

water\aqua\eau · butylene glycol · ethylhexyl methoxycrylene ·butyloctyl salicylate · dextrin palmitate · polymethylsilsesquioxane ·
glycerin · lactobacillus ferment lysate · aloe barbadensis leaf polysaccharides · sodium hyaluronate · caffeine · sodium
polyaspartate · 7-dehydrocholesterol · caprylyl glycol · acrylates copolymer · sorbitol · dimethicone · polyglyceryl-2 stearate · sucrose ·
saccharide isomerate · hydroxyethyl urea · ppg-8-ceteth-20 · sorbeth-30 tetraisostearate · glyceryl stearate · sorbitan
sesquiisostearate · potassium hydroxide · carbomer · dipropyleneglycol · dehydroxanthan gum · stearyl alcohol · sodium
polyacryloyldimethyl taurate · hexylene glycol · acrylates/beheneth-25 methacrylate copolymer · acrylates/c10-30 alkyl
acrylate crosspolymer · tocopheryl acetate · bht · disodium edta ·sodium citrate · citric acid · potassium sorbate · sodium
benzoate · phenoxyethanol · red 4 (ci 14700) [iln50856]

OTHER INFORMAITON

protect the product in this container from excessive heat and direct sun

PRINCIPAL DISPLAY PANEL

CLINIQUE
moisture surge
broad spectrum SPF 28
sheer hydrator
ALOE BIOFERMENT + PRO-VIT D
POIDS NET WT. 1.7 OZ./50 ml e